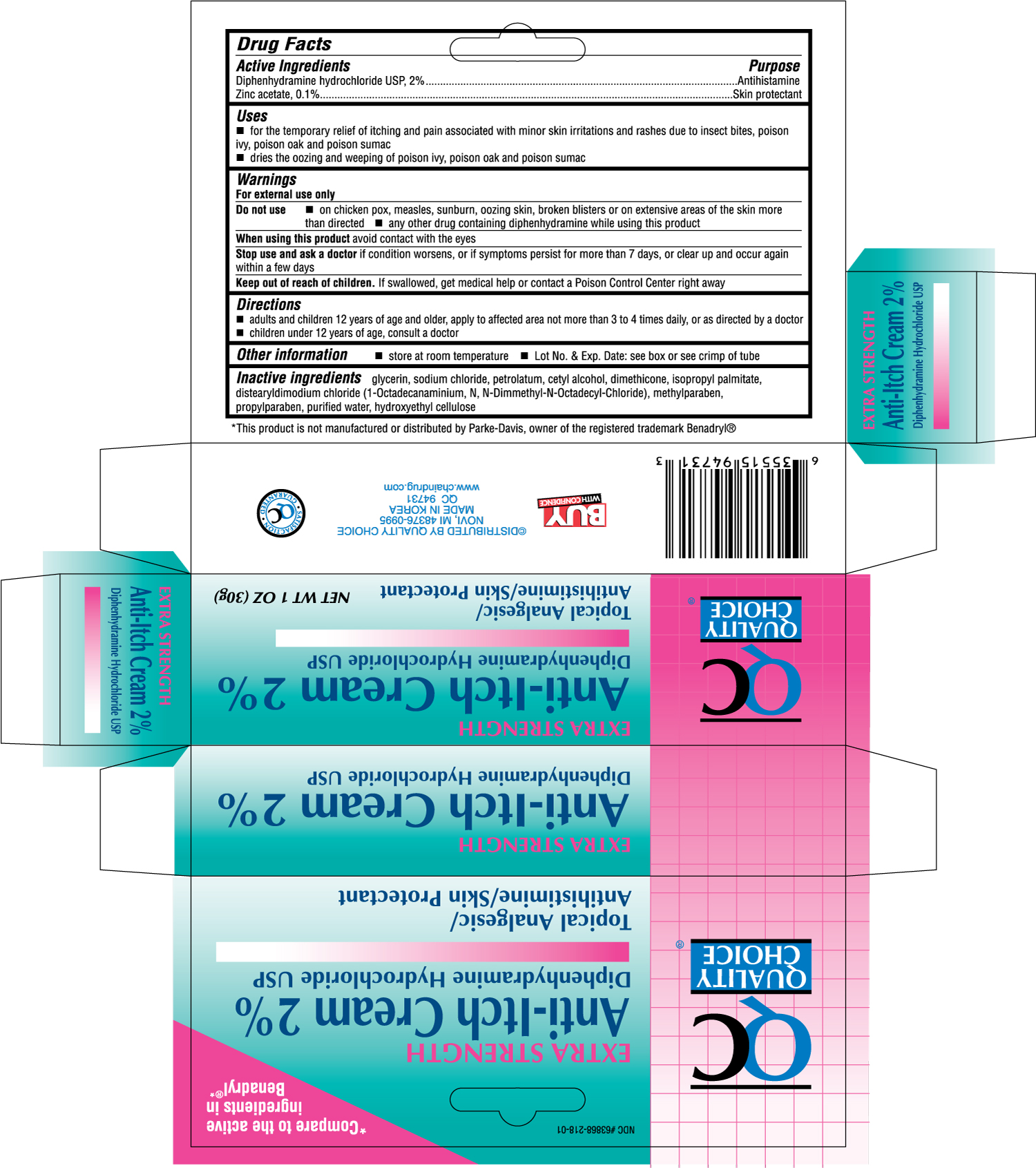 DRUG LABEL: QUALITY CHOICE EXTRA STRENGTH ANTI ITCH
NDC: 63868-947 | Form: CREAM
Manufacturer: CHAIN DRUG MARKETING ASSOCIATION INC
Category: otc | Type: HUMAN OTC DRUG LABEL
Date: 20120213

ACTIVE INGREDIENTS: DIPHENHYDRAMINE HYDROCHLORIDE 2 g/100 g; ZINC ACETATE 0.1 g/100 g
INACTIVE INGREDIENTS: GLYCERIN; SODIUM CHLORIDE; PETROLATUM; CETYL ALCOHOL; DIMETHICONE; ISOPROPYL PALMITATE; METHYLPARABEN; PROPYLPARABEN; WATER

Drug Facts

Active Ingredients Purpose

Diphenhydramine hydrochloride USP, 2%.............................................Antihistamine

Zinc acetate, 0.1%.............................................................................Skin protectant

Uses

- for the temporary relief of itching and pain associated with minor skin irritations and rashes due to insect bites, poison ivy, poison oak, and poison sumac
- dries the oozing and weeping of poison ivy, poison oak and poison sumac

Warnings

For external use only

Do not use

- on chicken pox, measles, sunburn, oozing skin, broken blisters or on extensive areas of the skin more than directed
- any other drug containing diphenhydramine while using this product

When using this product avoid contact with the eyes

Stop use and ask a doctor if condition worsens, or if symptoms persists for more than 7 days, or clear up and occur again within a few days

Keep out of reach of children. If swallowed, get medical help or contact a Poison Control Center right away

Directions

- adults and children 12 years of age and older,apply to affected area not more than 3 to 4 times daily, or as directed by a doctor
- children under 12 years of age, consult a doctor

Other information

- store at room temperature
- Lot No. and Exp. Date: see box or see crimp of tube

Inactive ingredients

glycerin, sodium chloride, petrolatum, cetyl alcohol, dimethicone, isopropyl palmitate, distearyldimodium chloride (1-Octadecanaminium, N, N-Dimmethyl-N-Octadecyl-Chloride), methylparaben, propylparaben, purified water, hydroxyethyl cellulose

DOSAGE AND ADMINISTRATION

DISTRIBUTED BY QUALITY CHOICE

NOVI, MI 48376-0995

MADE IN KOREA

QC 94731

www.chaindrug.com

PACKAGE LABEL

Enter section text here